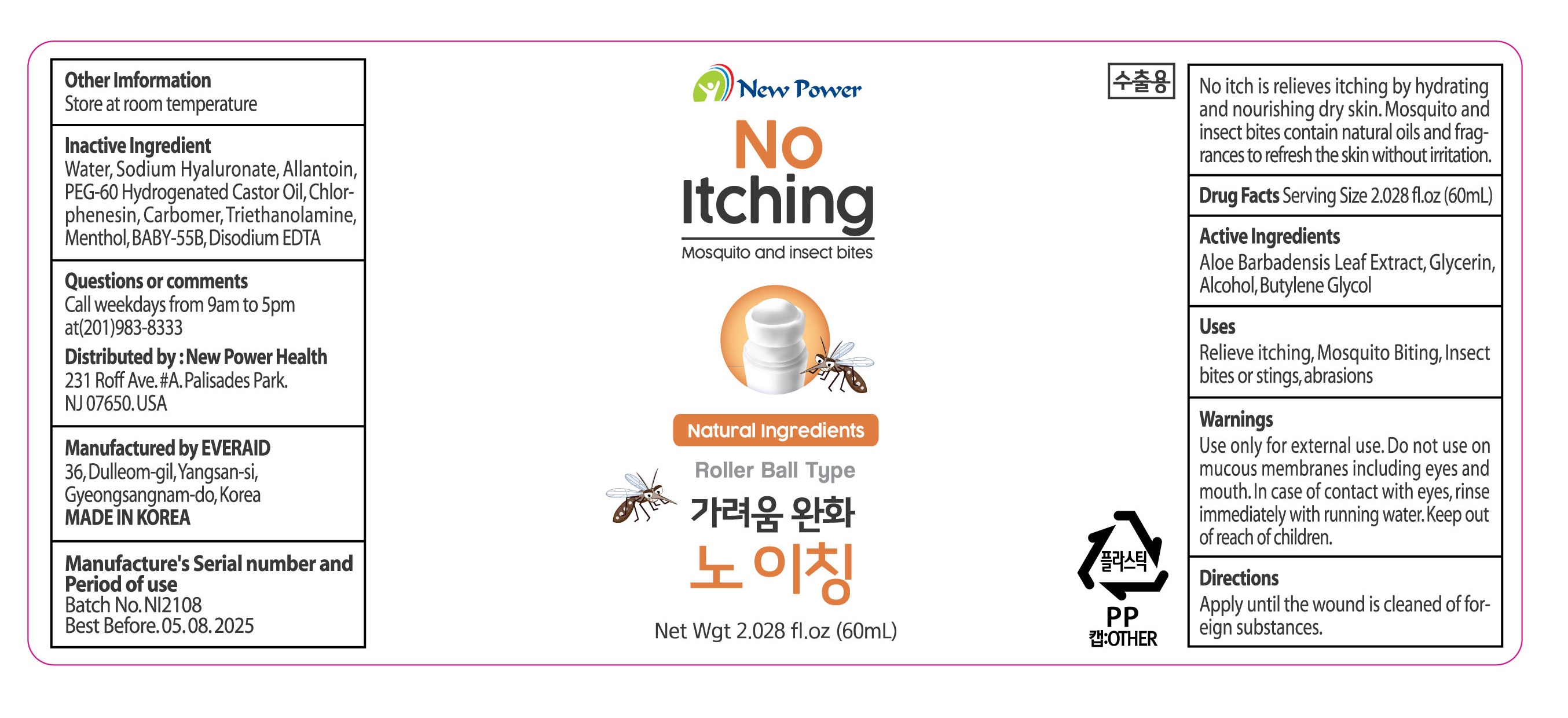 DRUG LABEL: NO itching
NDC: 82145-0003 | Form: LIQUID
Manufacturer: Aloe Vera Korea Co.,Ltd.
Category: otc | Type: HUMAN OTC DRUG LABEL
Date: 20210803

ACTIVE INGREDIENTS: GLYCERIN 8 g/100 mL
INACTIVE INGREDIENTS: WATER; ALLANTOIN

Drug Facts

ACTIVE INGREDIENT

glycerin

INACTIVE INGREDIENT

WATER, ALCOHOL, BUTYLENE GLYCOL, ETC

PURPOSE

for skin protectant

relieve itchiness by providing moisture and nutrients to the dry skin

keep out of reach of the children

INDICATIONS AND USAGE

shake the container for 2 to 3 times before use, apply it evenly

WARNINGS

■ if following abnormal symptoms occurs after use , stop use and consult with a skin specialist

red specks, swelling, itching

■ don’t use on the part where there is injury, eczema, or dermatitis

Keep out of reach of children

■ if swallowed, get medical help or contact a person control center immediately

DOSAGE AND ADMINISTRATION

for external use only